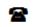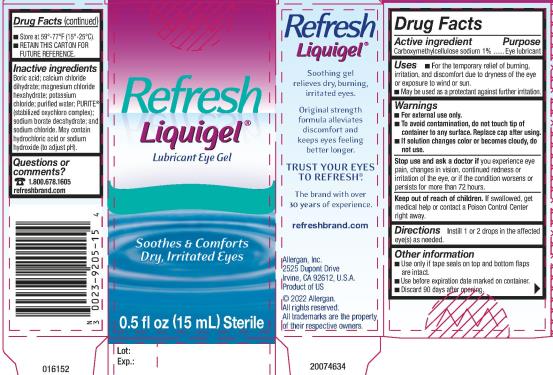 DRUG LABEL: REFRESH LIQUIGEL
NDC: 0023-9205 | Form: GEL
Manufacturer: Allergan, Inc.
Category: otc | Type: HUMAN OTC DRUG LABEL
Date: 20221111

ACTIVE INGREDIENTS: CARBOXYMETHYLCELLULOSE SODIUM, UNSPECIFIED 10 mg/1 mL
INACTIVE INGREDIENTS: BORIC ACID; CALCIUM CHLORIDE; MAGNESIUM CHLORIDE; POTASSIUM CHLORIDE; WATER; SODIUM BORATE; SODIUM CHLORIDE; SODIUM CHLORITE; HYDROCHLORIC ACID; SODIUM HYDROXIDE

REFRESH LIQUIGEL®
Drug Facts

Active ingredient

Carboxymethylcellulose sodium 1%

Purpose

Eye lubricant

Uses

- For the temporary relief of burning, irritation, and discomfort due to dryness of the eye or exposure to wind or sun.
- May be used as a protectant against further irritation.

Warnings

- For external use only.
- To avoid contamination, do not touch tip of container to any surface. Replace cap after using.
- If solution changes color or becomes cloudy, do not use.

Stop use and ask a doctor if

you experience eye pain, changes in vision, continued redness or irritation of the eye, or if the condition worsens or persists for more than 72 hours.

Keep out of reach of children.

If swallowed, get medical help or contact a Poison Control Center right away.

Directions

Instill 1 or 2 drops in the affected eye(s) as needed.

Other information

- Use only if tape seals on top and bottom flaps are intact.
- Use before expiration date marked on container.
- Discard 90 days after opening.
- Store at 59°-77°F (15°-25°C).
- RETAIN THIS CARTON FOR FUTURE REFERENCE.

Inactive ingredients

Boric acid; calcium chloride dihydrate; magnesium chloride hexahydrate; potassium chloride; purified water; PURITE® (stabilized oxychloro complex); sodium borate decahydrate; and sodium chloride. May contain hydrochloric acid or sodium hydroxide (to adjust pH).

Questions or comments?

1.800.687.1605

refreshbrand.com

v1.0DFL9205

PRINCIPAL DISPLAY PANEL

NDC 0023-9205-15
Refresh
Liquigel®
Lubricant Eye Gel
Soothes & Comforts
Dry, Irritated Eyes
0.5 fl oz (15 mL) Sterile